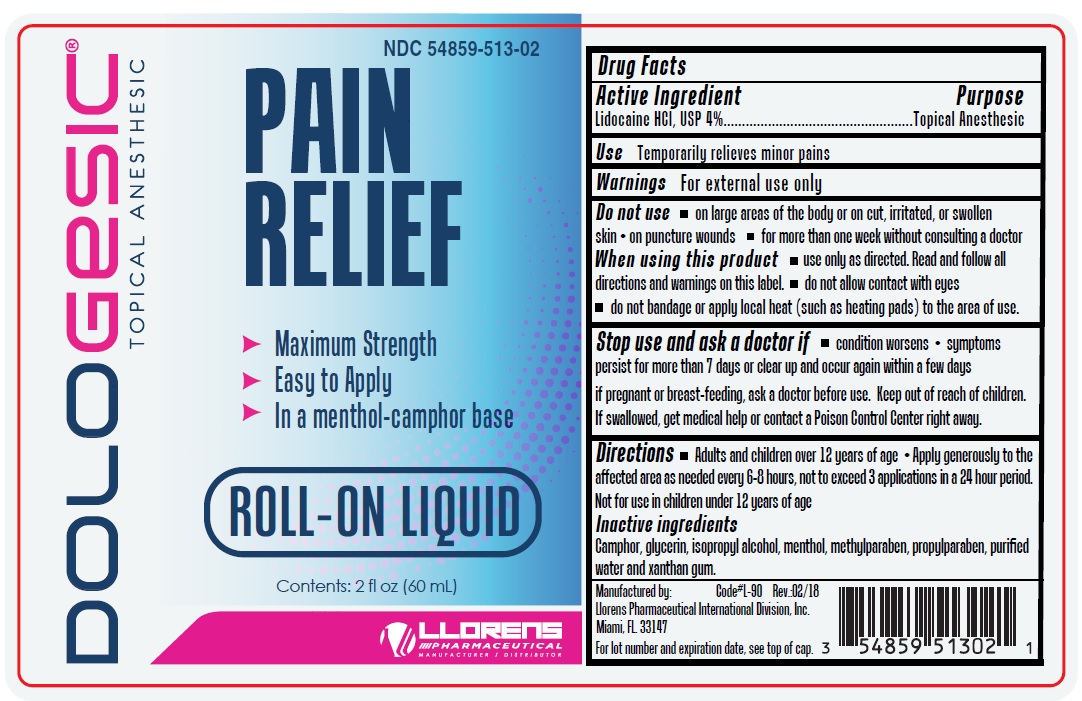 DRUG LABEL: Dologesic Roll-On
NDC: 54859-513 | Form: LIQUID
Manufacturer: Llorens Pharmaceutical International Division, Inc.
Category: otc | Type: HUMAN OTC DRUG LABEL
Date: 20251231

ACTIVE INGREDIENTS: LIDOCAINE HYDROCHLORIDE 4 g/100 mL
INACTIVE INGREDIENTS: CAMPHOR (SYNTHETIC); GLYCERIN; ISOPROPYL ALCOHOL; MENTHOL; METHYLPARABEN; PROPYLPARABEN; WATER; XANTHAN GUM

Dologesic Roll-On 513

Active Ingredient

Lidocaine HCL, USP 4%

Purpose

Topical Anesthetic

Use

Temporarily relieves minor pains

Warnings

For external use only

Do not use

- on large areas of the body or on cut, irritated or swollen skin
- on puncture wounds
- for more than one week without consulting a doctor

When using this product

- use only as directed. Read and follow all directions and warnings on this label.
- do not allow contact with eyes
- do not bandage or apply local heat (such as heating pads) to the area of use.

Stop use and ask doctor if

- condition worsens
- symptoms persist for more than 7 days or clear up and occur again within a few days

PREGNANCY OR BREAST FEEDING

If pregnant or breast-feeding, ask a doctor before use.

Keep out of reach of children. If swallowed, get medical help or contact a Poison Control Center right away.

Directions

- Adults and children over 12 years of age
- Apply generously to the affected area as needed every 6-8 hours, not to exceed 3 application in a 24 hour period.
- Not for use in children under 12 years of age.

Inactive ingredients

camphor, glycerin, isopropyl alcohol, menthol, methylparaben, propylparaben, purified water and xantham gum.

Questions

Llorens Pharmaceutical International Division, Inc.

Miami Fl 33147